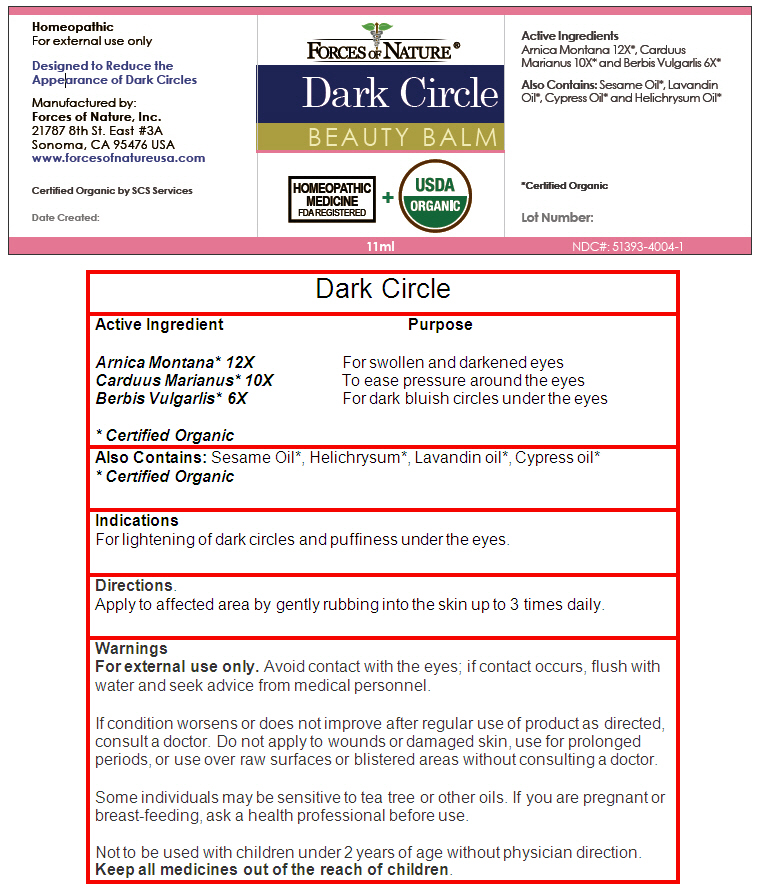 DRUG LABEL: Dark Circle
NDC: 51393-4004 | Form: SOLUTION/ DROPS
Manufacturer: Forces of Nature
Category: homeopathic | Type: HUMAN OTC DRUG LABEL
Date: 20140103

ACTIVE INGREDIENTS: Arnica Montana 12 [hp_X]/100 mL; Milk Thistle 10 [hp_X]/100 mL; Berberis Vulgaris Fruit 6 [hp_X]/100 mL
INACTIVE INGREDIENTS: Lavender Oil; Helichrysum Italicum Flowering Top; Cupressus Sempervirens Leaf Oil; Sesame Oil

Dark Circle

ACTIVE INGREDIENT

Active Ingredient | Purpose
Arnica Montana [Certified Organic] 12X | For swollen and darkened eyes
Carduus Marianus 10X | To ease pressure around the eyes
Berbis Vulgarlis 6X | For dark bluish circles under the eyes

Also Contains

Sesame Oil [Certified Organic] , Helichrysum, Lavandin oil, Cypress oil

Indications

For lightening of dark circles and puffiness under the eyes.

Directions

Apply to affected area by gently rubbing into the skin up to 3 times daily.

Warnings

For external use only. Avoid contact with the eyes; if contact occurs, flush with water and seek advice from medical personnel.

ASK DOCTOR

If condition worsens or does not improve after regular use of product as directed, consult a doctor. Do not apply to wounds or damaged skin, use for prolonged periods, or use over raw surfaces or blistered areas without consulting a doctor.

Some individuals may be sensitive to tea tree or other oils.

PREGNANCY OR BREAST FEEDING

If you are pregnant or breast-feeding, ask a health professional before use.

KEEP OUT OF REACH OF CHILDREN

Not to be used with children under 2 years of age without physician direction. Keep all medicines out of the reach of children.

Manufactured by:
Forces of Nature, Inc.
21787 8th St. East #3A
Sonoma, CA 95476 USA

PRINCIPAL DISPLAY PANEL - 11 ml Bottle Label

FORCES OF NATURE ®

Dark Circle
BEAUTY BALM

HOMEOPATHIC
MEDICINE
FDA REGISTERED
+
USDA
ORGANIC

11ml